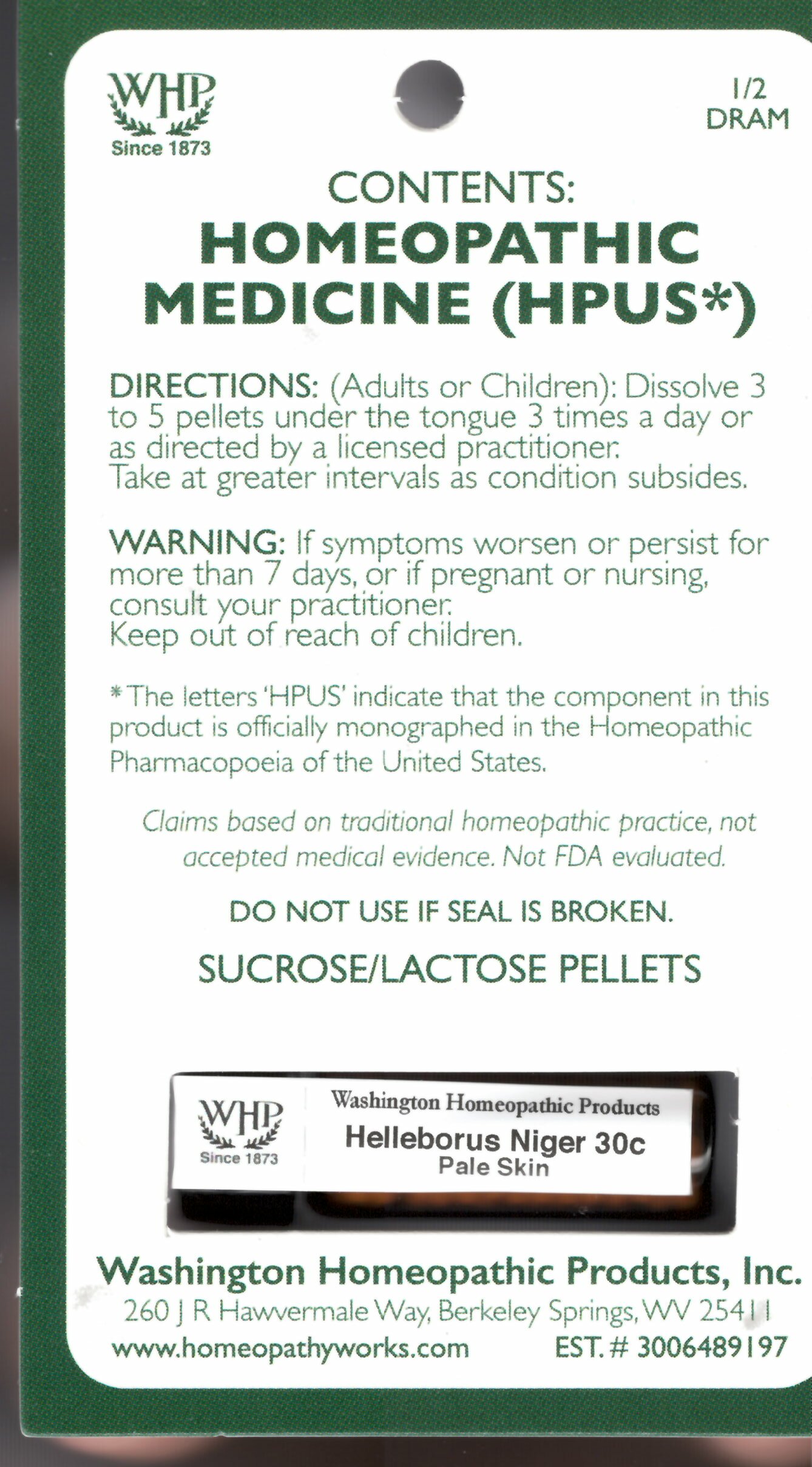 DRUG LABEL: Helleborus niger
NDC: 71919-817 | Form: PELLET
Manufacturer: Washington Homeopathic Products
Category: homeopathic | Type: HUMAN OTC DRUG LABEL
Date: 20250128

ACTIVE INGREDIENTS: HELLEBORUS NIGER ROOT 30 [hp_C]/1 1
INACTIVE INGREDIENTS: SUCROSE; LACTOSE

Helleborus niger Kit Refill 30c

ACTIVE INGREDIENTS

Helleborus niger 30C

USES

Indicated for Pale skin.

KEEP OUT OF REACH OF CHILDREN

As with all medications, keep out of reach of children.

INDICATIONS

Helleborus niger indicated for Pale Skin.

STOP USE AND ASK DOCTOR

If symptoms persist or recur, discontinue use. If pregnant or nursing, consult a licensed practitioner before using this product.

DIRECTIONS

(Adults or Children): Dissolve 3 to 5 pellets under tongue 3 times a day or as directed by a licensed practitioner. Take at greater intervals as condition subsides.

INACTIVE INGREDIENTS

Sucrose/Lactose